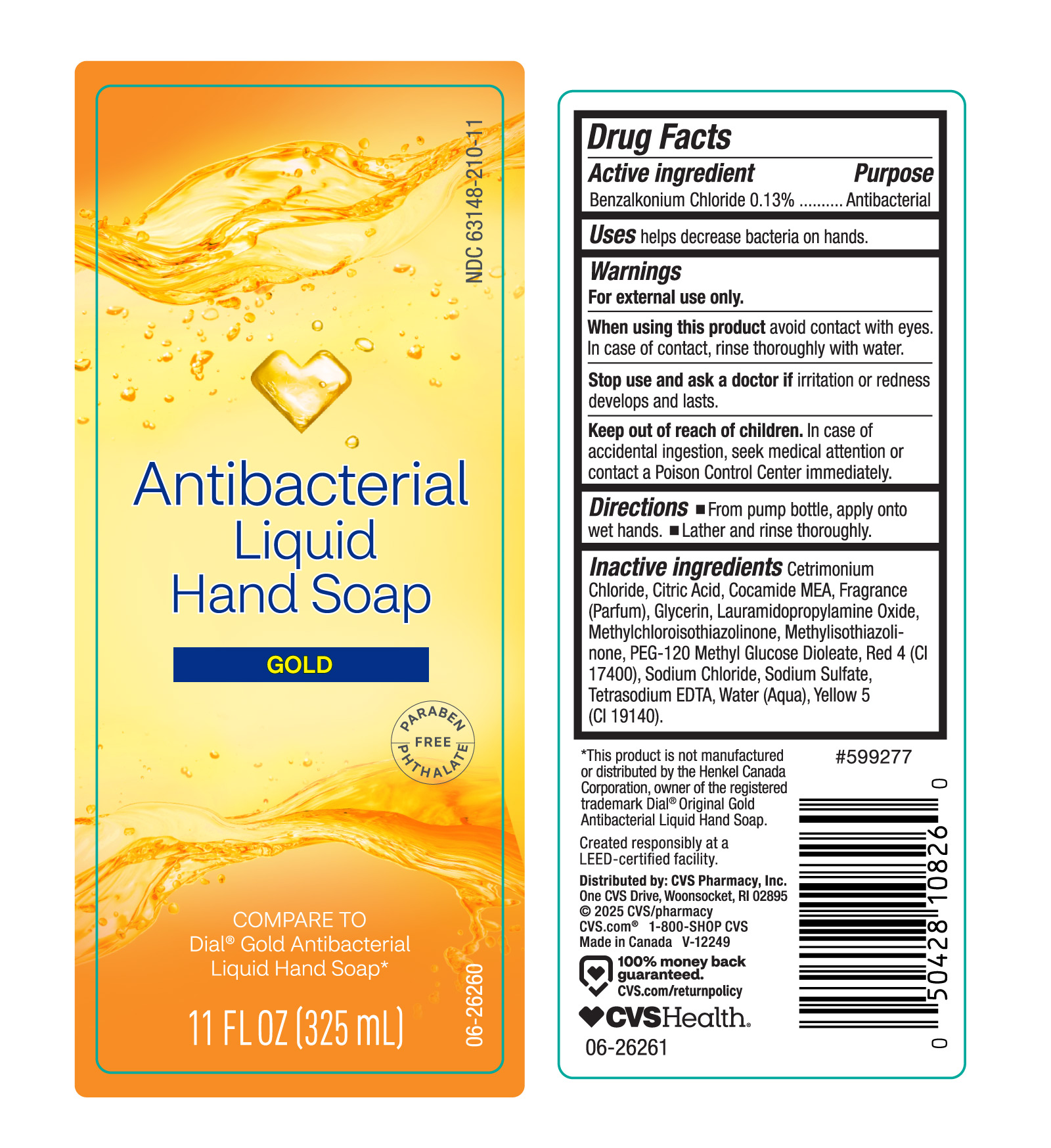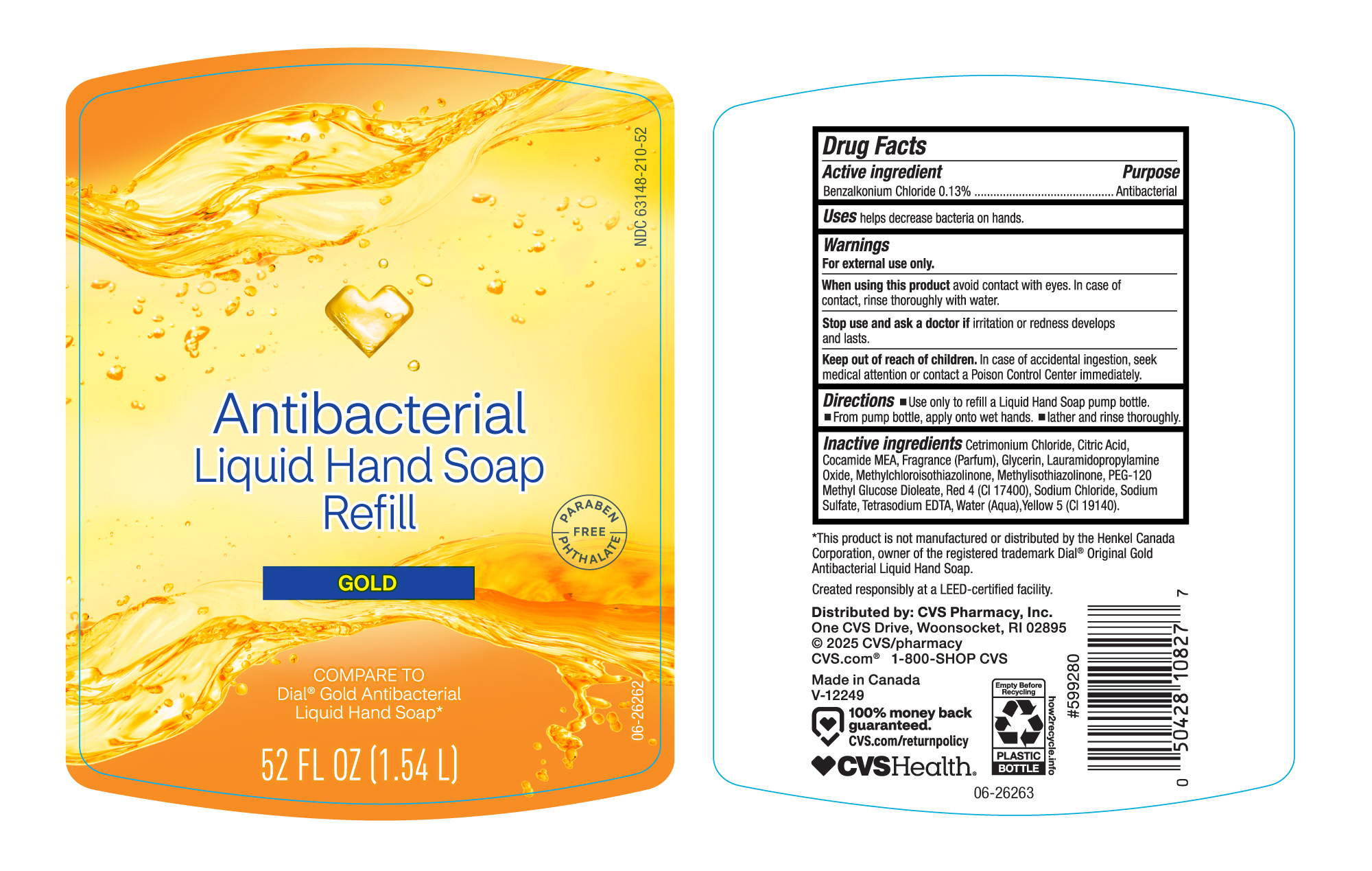 DRUG LABEL: Gold LHS
NDC: 63148-210 | Form: LIQUID
Manufacturer: Apollo Health and Beauty Care
Category: otc | Type: HUMAN OTC DRUG LABEL
Date: 20241105

ACTIVE INGREDIENTS: BENZALKONIUM CHLORIDE 130 mg/100 mL
INACTIVE INGREDIENTS: CITRIC ACID; COCAMIDE MEA; FRAGRANCE CLEAN ORC0600327; GLYCERIN; LAURAMIDOPROPYLAMINE OXIDE; METHYLCHLOROISOTHIAZOLINONE; PEG-120 METHYL GLUCOSE DIOLEATE; RED 4; SODIUM CHLORIDE; SODIUM SULFATE; WATER; FRESHWATER CLAM; YELLOW 5; METHYLISOTHIAZOLINONE; CETRIMONIUM CHLORIDE

NDC-63148-210. Antibac LHS

Active Ingredients

Benzalkonium Chloride (0.13%)

Purpose

Antibacterial

Uses

Helps decrease bacteria on hands.

Warnings

When using the product

Avoid contact with eyes. In case of contact, rinse thoroughly with water.

Stop use and ask a doctor if

irritation or redness develops and lasts.

Keep out of reach of children

In case of accidental ingestion, seek medical attention or contact a Poison Control Center immediately.

Directions

- From pump bottle, apply onto wet hands.
- Lather and rinse thoroughly.

Inactive Ingredients

Cetrimonium Chloride, Citric Acid, Cocamide MEA, Fragrance (Parfum), Glycerin, Lauramidopropylamine Oxide, Methylchloroisothiazolinone, Methylisothiazolinone, PEG-120 Methyl Glucose Dioleate, Red 4 (CI17400), Sodium Chloride, Sodium Sulfate, Tetrasodium EDTA, Wate (Aqua), Yellow (CI19140).